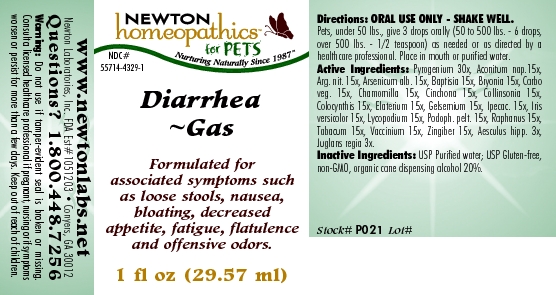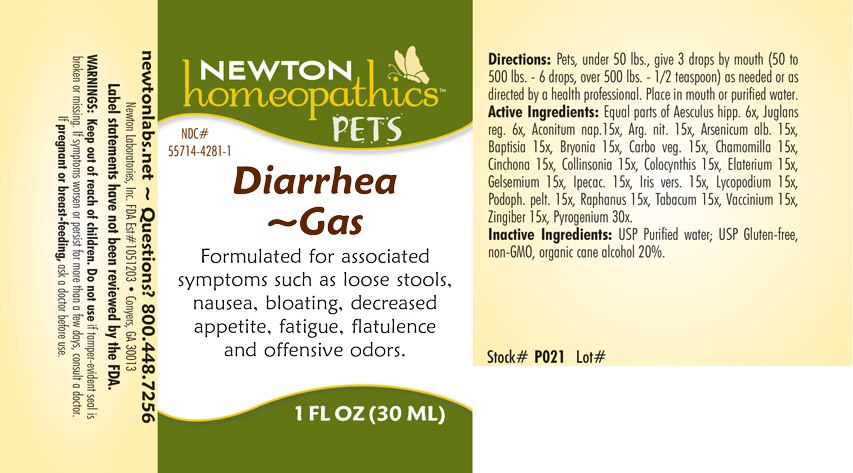 DRUG LABEL: Diarrhea - Gas
NDC: 55714-4329 | Form: LIQUID
Manufacturer: Newton Laboratories, Inc.
Category: homeopathic | Type: OTC ANIMAL DRUG LABEL
Date: 20190114

ACTIVE INGREDIENTS: Rancid Beef 30 [hp_X]/1 mL; Aconitum Napellus 15 [hp_X]/1 mL; Silver Nitrate 15 [hp_X]/1 mL; Arsenic Trioxide 15 [hp_X]/1 mL; Baptisia Tinctoria 15 [hp_X]/1 mL; Bryonia Alba Root 15 [hp_X]/1 mL; Activated Charcoal 15 [hp_X]/1 mL; Matricaria Recutita 15 [hp_X]/1 mL; Cinchona Officinalis Bark 15 [hp_X]/1 mL; Collinsonia Canadensis Root 15 [hp_X]/1 mL; Citrullus Colocynthis Fruit Pulp 15 [hp_X]/1 mL; Ecballium Elaterium Fruit 15 [hp_X]/1 mL; Gelsemium Sempervirens Root 15 [hp_X]/1 mL; Ipecac 15 [hp_X]/1 mL; Iris Versicolor Root 15 [hp_X]/1 mL; Lycopodium Clavatum Spore 15 [hp_X]/1 mL; Podophyllum 15 [hp_X]/1 mL; Radish 15 [hp_X]/1 mL; Tobacco Leaf 15 [hp_X]/1 mL; Bilberry 15 [hp_X]/1 mL; Ginger 15 [hp_X]/1 mL; Horse Chestnut 3 [hp_X]/1 mL; Juglans Regia Leaf 3 [hp_X]/1 mL
INACTIVE INGREDIENTS: Alcohol

Diarrhea - Gas

INDICATIONS & USAGE SECTION

Diarrhea - Gas Formulated for associated symptoms such as loose stools, nausea, bloating, decreased appetite, fatigue, flatulence and offensive odors.

DOSAGE & ADMINISTRATION SECTION

Directions: Pets, under 50 lbs., give 3 drops by mouth (50 to 500 lbs. - 6 drops, over 500 lbs. - 1/2 teaspoon) as needed or as directed by a health professional. Place in mouth or purified water.

OTC - ACTIVE INGREDIENT SECTION

Equal parts of Aesculus hipp. 3x, Juglans regia 3x, Aconitum nap.15x, Arg. nit. 15x, Arsenicum alb. 15x, Baptisia 15x, Bryonia 15x, Carbo veg. 15x, Chamomilla 15x, Cinchona 15x, Collinsonia 15x, Colocynthis 15x, Elaterium 15x, Gelsemium 15x, Ipecac. 15x, Iris versicolor 15x, Lycopodium 15x, Podoph. pelt. 15x, Raphanus 15x, Tabacum 15x, Vaccinium 15x, Zingiber 15x, Pyrogenium 30x .

OTC - PURPOSE SECTION

Formulated for associated symptoms such as loose stools, nausea, bloating, decreased appetite, fatigue, flatulence and offensive odors.

INACTIVE INGREDIENT SECTION

Inactive Ingredients: USP Purified Water; USP Gluten-free, non-GMO, organic cane alcohol 20%.

QUESTIONS SECTION

newtonlabs.net Questions? 1.800.448.7256
Newton Laboratories, Inc. FDA Est # 1051203 - Conyers, GA 30013

WARNINGS SECTION

WARNINGS: Keep out of reach of children. Do not use if tamper-evident seal is broken or missing. If symptoms worsen or persist for more than a few days, consult a doctor. If pregnant or breast-feeding, ask a doctor before use.

OTC - PREGNANCY OR BREAST FEEDING SECTION

If pregnant or breast-feeding, ask a doctor before use.

OTC - KEEP OUT OF REACH OF CHILDREN SECTION

Keep out of reach of children.